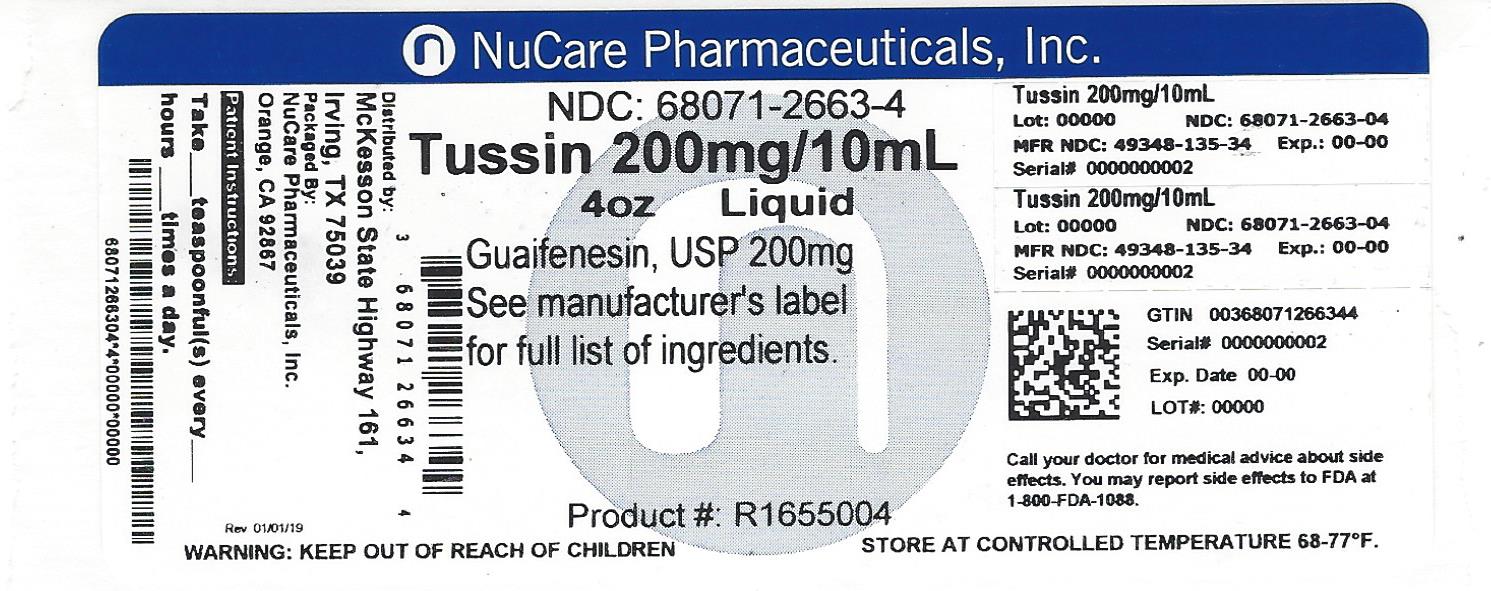 DRUG LABEL: Tussin
NDC: 68071-2663 | Form: SOLUTION
Manufacturer: NuCare Pharmaceuticals,Inc.
Category: otc | Type: HUMAN OTC DRUG LABEL
Date: 20220328

ACTIVE INGREDIENTS: GUAIFENESIN 200 mg/10 mL
INACTIVE INGREDIENTS: ANHYDROUS CITRIC ACID; CARAMEL; FD&C RED NO. 40; GLYCERIN; HIGH FRUCTOSE CORN SYRUP; PROPYLENE GLYCOL; WATER; SACCHARIN SODIUM; SODIUM BENZOATE; MENTHOL, UNSPECIFIED FORM

McKesson Adult Tussin Drug Facts

Active ingredient (in each 10 mL)

Guaifenesin, USP 200 mg

Purpose

Expectorant

Use

helps loosen phlegm (mucus) and thin bronchial secretions to make coughs more productive

Warnings

Ask a doctor before use if you have

- cough that occurs with too much phlegm (mucus)
- cough that lasts or is chronic such as occurs with smoking, asthma, chronic bronchitis, or emphysema

Stop use and ask a doctor if

cough lasts for more than 7 days, comes back, or is accompanied by fever, rash, or persistent headache. A persistent cough may be a sign of a serious condition.

If pregnant or breast-feeding,

ask a health professional before use.

Keep out of reach of children.

In case of overdose, get medical help or contact a Poison Control Center right away (1-800-222-1222).

Directions

- do not take more than 6 doses in any 24-hour period
- measure only with dosing cup provided
- keep dosing cup with product
- mL = milliliter
- this adult product is not intended for use in children under 12 years of age

age | dose
adults and children 12 years and over | 10 – 20 mL every 4 hours
children under 12 years | do not use

Other information

- store at 20-25°C (68-77°F). Do not refrigerate.

Inactive ingredients

anhydrous citric acid, caramel, FD&C red no. 40, flavor, glycerin, high fructose corn syrup, menthol, propylene glycol, purified water, saccharin sodium, sodium benzoate

Questions or comments?

1-800-719-9260